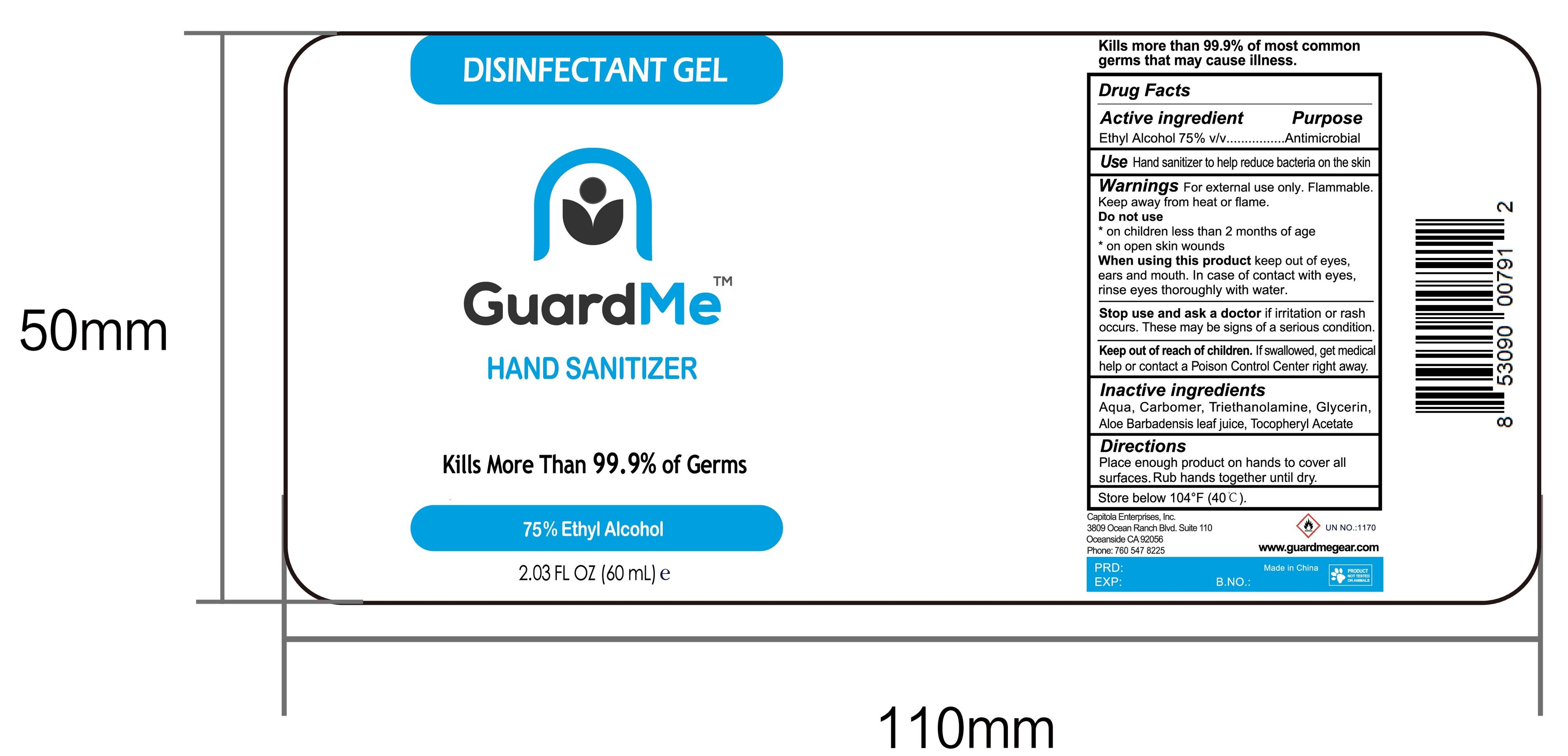 DRUG LABEL: GuardMe Hand Sannitizer
NDC: 73027-209 | Form: GEL
Manufacturer: JIANGSU HANHE DAILY CHEMICALS CO., LTD.
Category: otc | Type: HUMAN OTC DRUG LABEL
Date: 20211102

ACTIVE INGREDIENTS: ALCOHOL 75 mL/100 mL
INACTIVE INGREDIENTS: CARBOMER 940; TROLAMINE; GLYCERIN; ALOE VERA LEAF; .ALPHA.-TOCOPHEROL ACETATE

ACTIVE INGREDIENT

Ethyl Alcohol 75% v/v

Purpose

Antimicrobial

Use

Hand sanitizer to help reduce bacteria on the skin

Warnings

For external use only.

Non Medical. Flammable. Keep away from fire or flame

When using this product, keep out of eyes, ears, and mouth. In case of contact with eyes, rinse eyes thoroughly with water

Stop use and consult a doctor if irritation or rash occurs. This may be a sign of seriuous condition

Keep out of reach of children. If swallowed, get medical help or contact a poison control center right away

Directions

- Put enough products on your plam to cover all surfaces. Rub hands together until dry

Inactive ingredients

Water, Carbomer, Triethanolamine, Glycerin, Aloe Barbadensis Leaf Juice, Tocopheryl Acetate